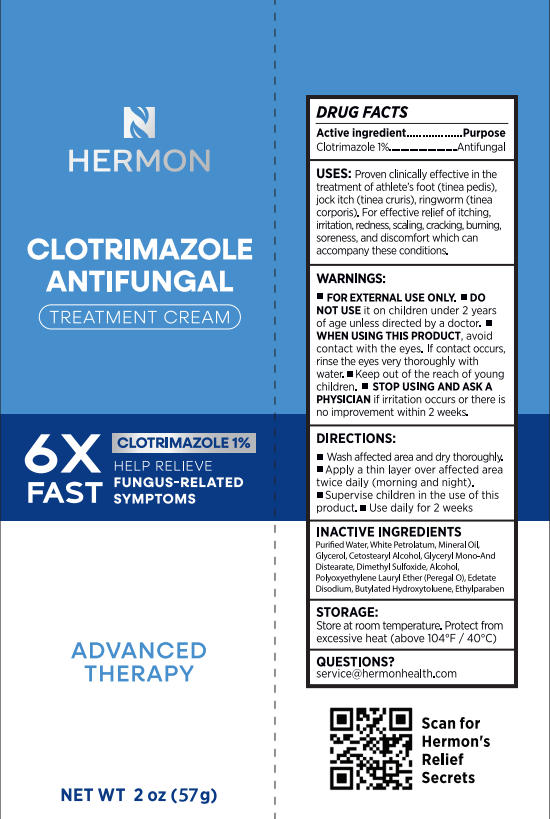 DRUG LABEL: Hermon Clotrimazole antifungal treatment cream
NDC: 85398-010 | Form: CREAM
Manufacturer: Beautivity LLC
Category: otc | Type: HUMAN OTC DRUG LABEL
Date: 20260302

ACTIVE INGREDIENTS: CLOTRIMAZOLE 0.57 g/57 g
INACTIVE INGREDIENTS: BUTYLATED HYDROXYTOLUENE; GLYCEROL FORMAL; ALCOHOL; WHITE PETROLATUM; CETOSTEARYL ALCOHOL; EDETATE DISODIUM; DIMETHYL SULFOXIDE; ETHYLPARABEN; WATER; MINERAL OIL

Update-85398-010-01

ACTIVE INGREDIENT

Cotrimazole 1%

PURPOSE

Antifungal

DOSAGE AND ADMINISTRATION

Proven clinically effective in the treatment of athlete's foot (tinea pedis), jock itch (tinea cruris), ringworm (tineacorporis). For effective relief of itching, irritation, redness, scaling, cracking, burning, soreness, and discomfort which can accompany these conditions.

WARNINGS

For external use only.

Do not use on children under 2 years of age unless directed by a doctor.

WHEN USING

avoide contact with eyes, if contact occurs, rinse thoroughly with water.

ASK DOCTOR

if irritation occurs or if there is no improvement within 2 weeks.

KEEP OUT OF REACH OF CHILDREN

in case of accidental ingestion, seek medical advice immediately or contact a Poison Control Center right away.
(1-800-222-1222)

INDICATIONS AND USAGE

- Wash affected area & dry thoroughly.
- Apply a thin layer over affected area twice daily (morning andnight).
- Supervise children in the use of this product.
- Use daily for 2 weeks.

INACTIVE INGREDIENT

Purifed Water, White Petrolatum, Mineral Oil, Glycerol, Cetostearyl Alcohol, Glyceryl Mono-And Distearate, Dimethyl sulfoxide, Alcohol, Polyoxyethylene Lauryl Ether (Peregal O), Edetate Disodium, Butylated Hydroxytoluene, Ethylparaben

STORAGE AND HANDLING

Store at room temperature, Protect from excessive heat (above 104°F/40°C)

QUESTIONS

visit us at www.hermonhealth.com